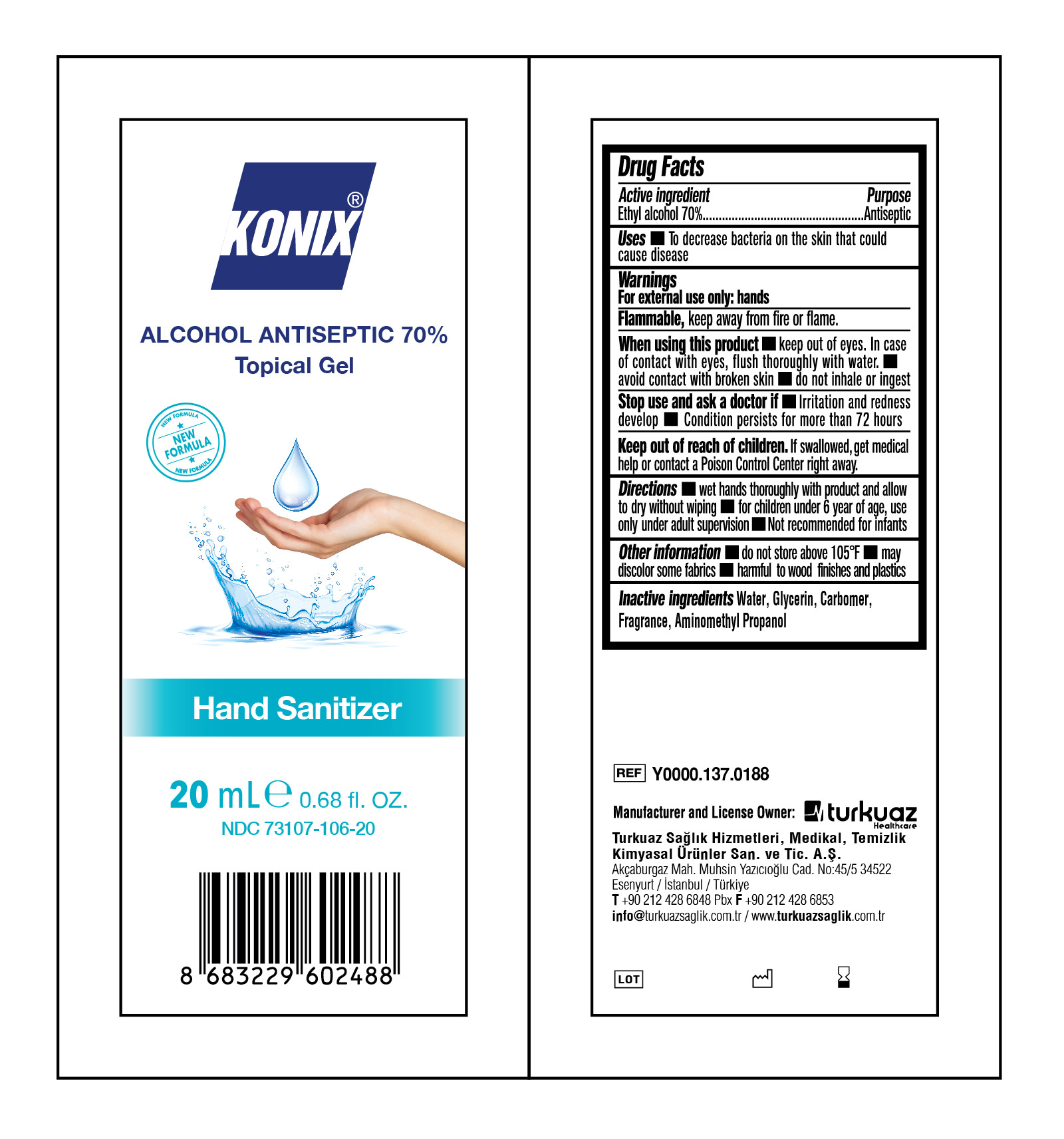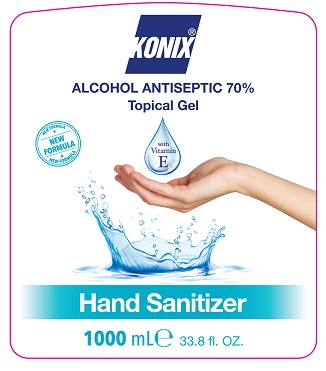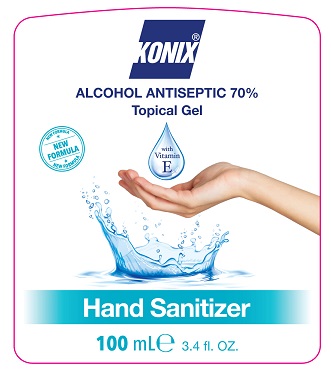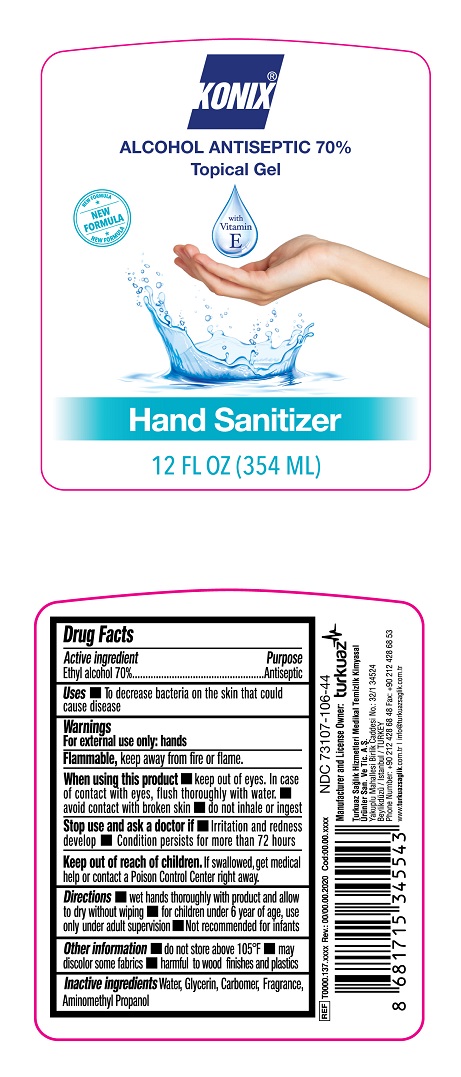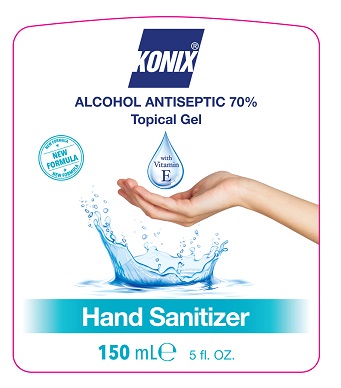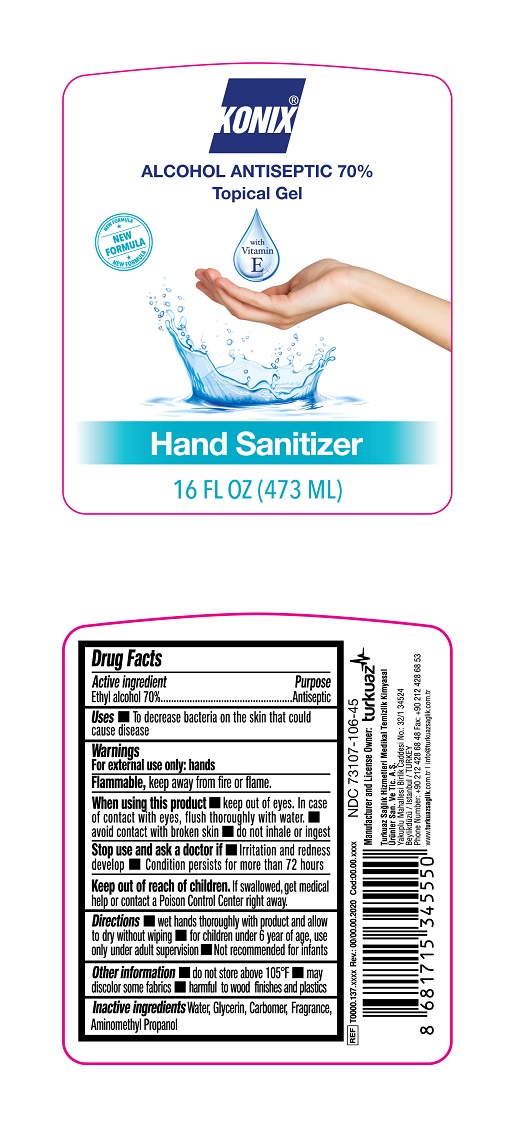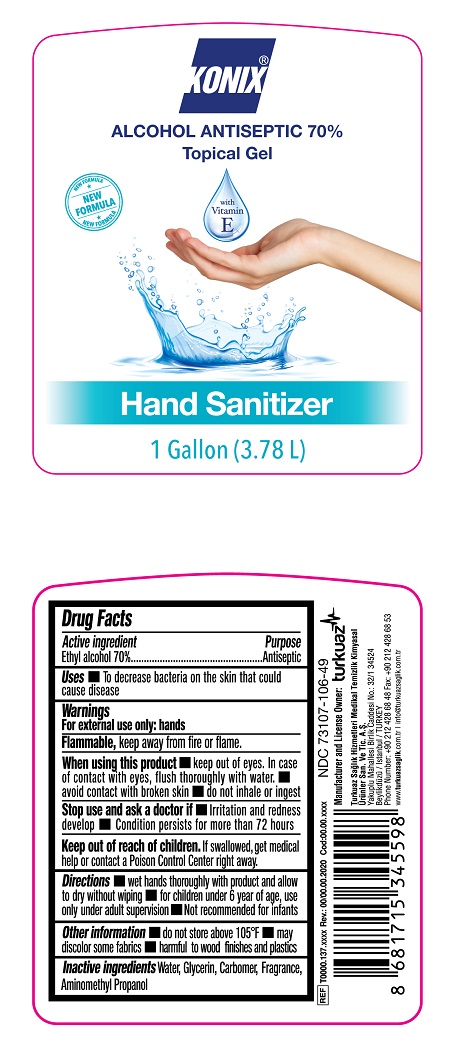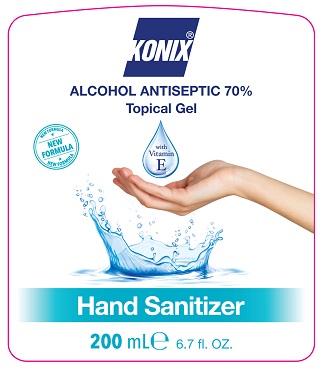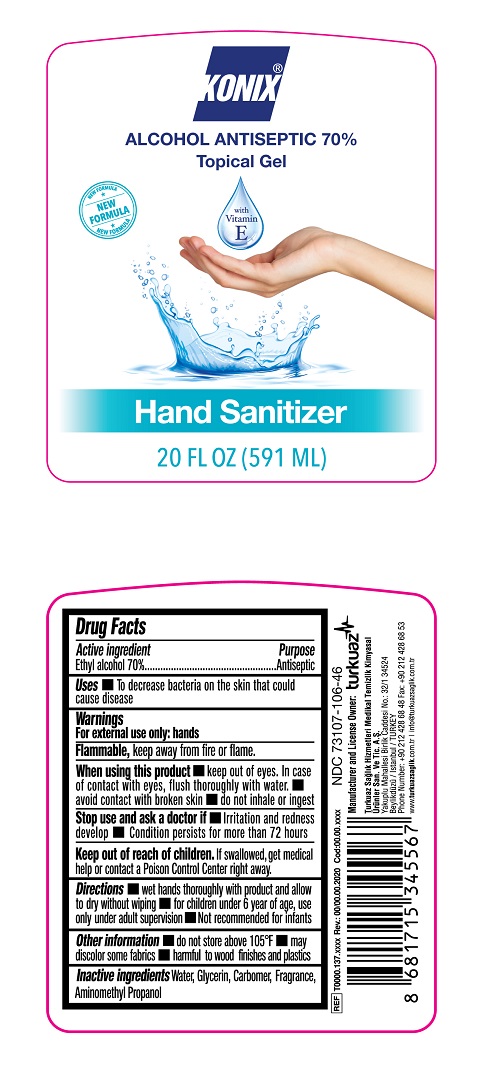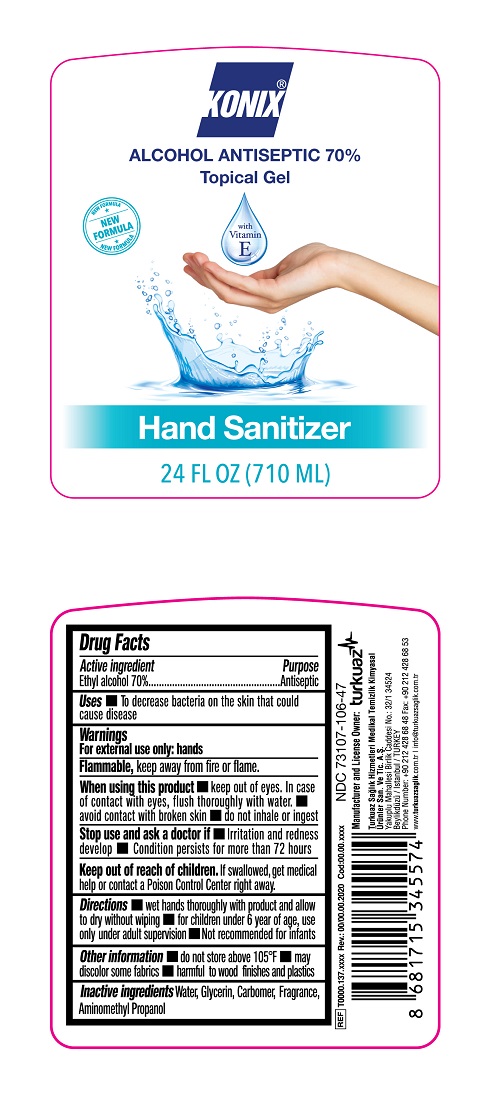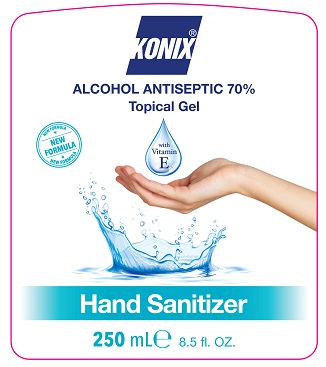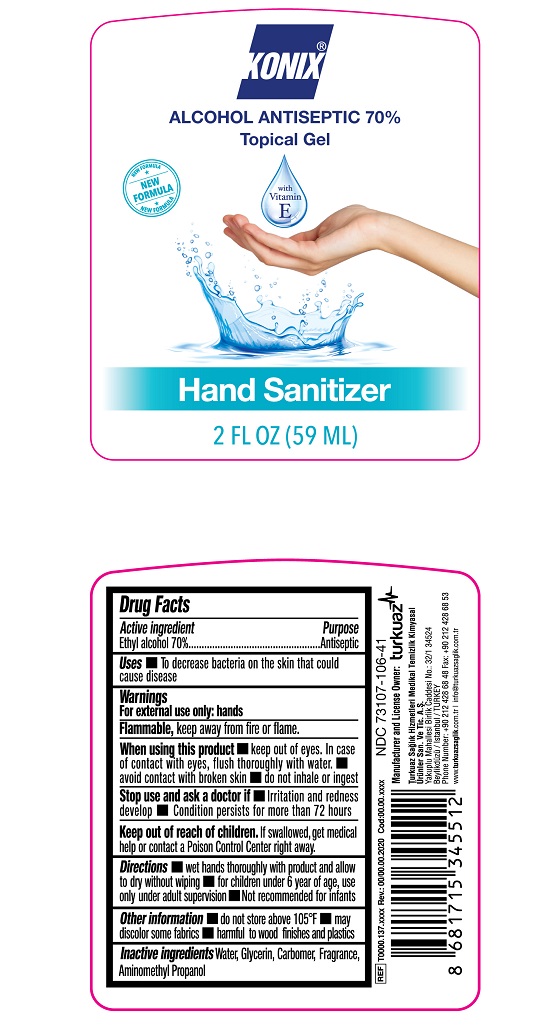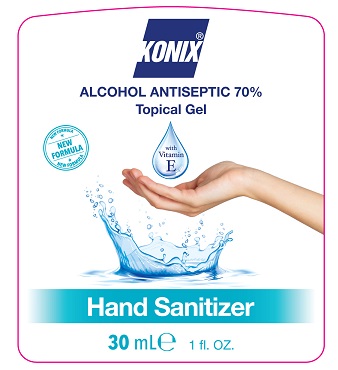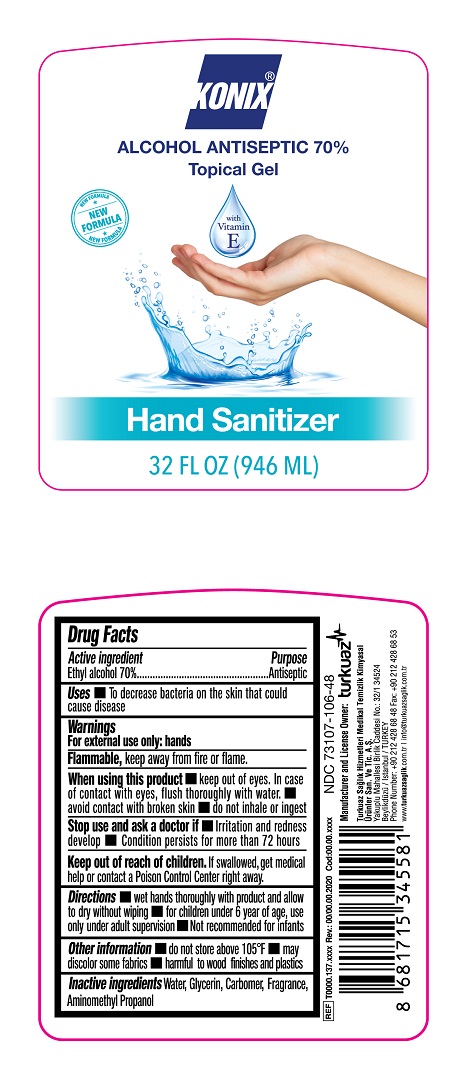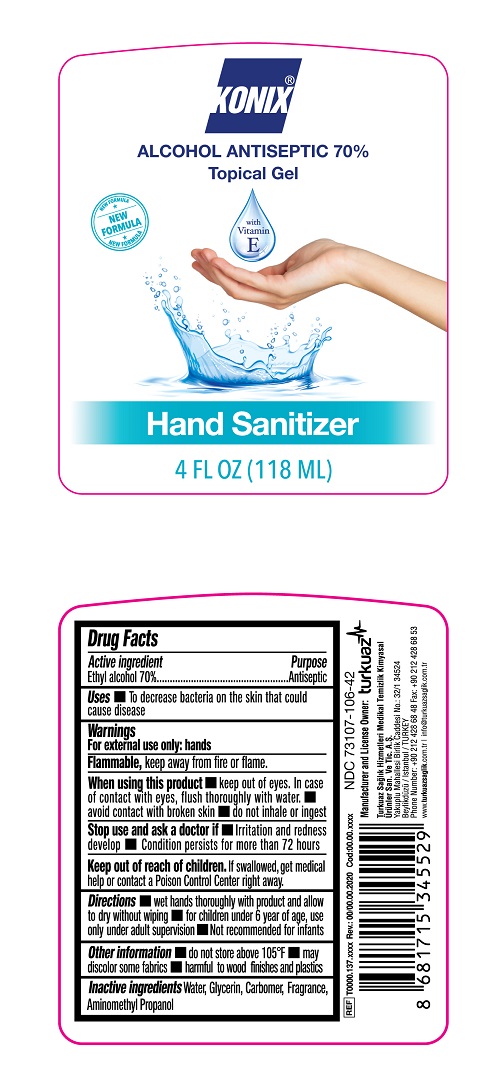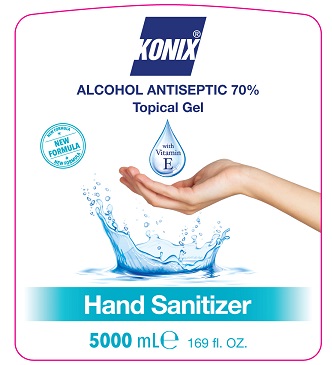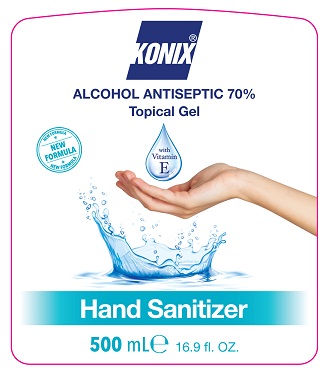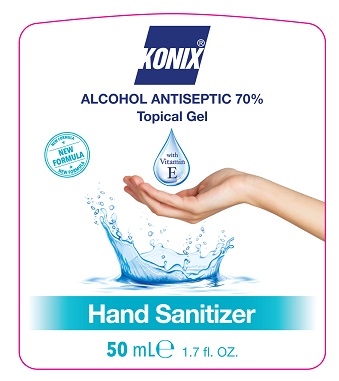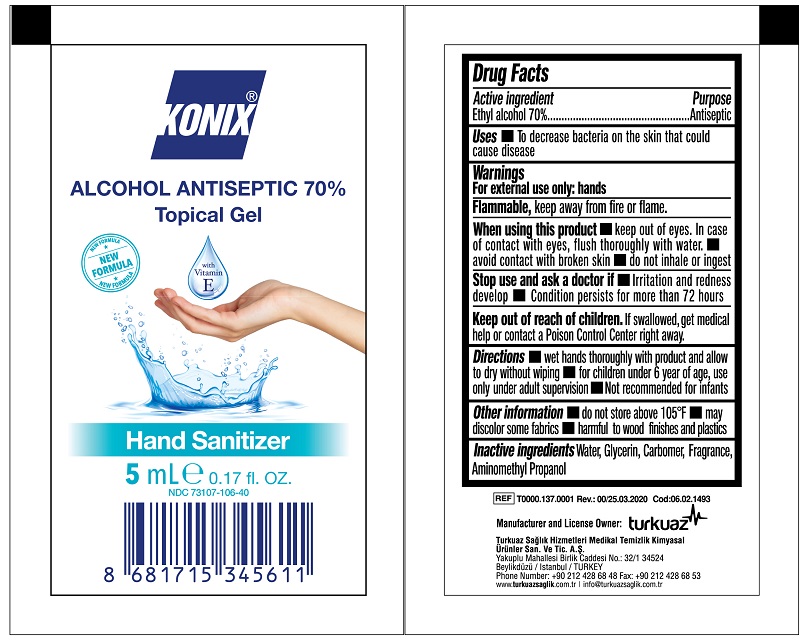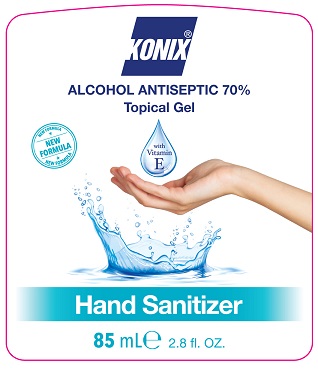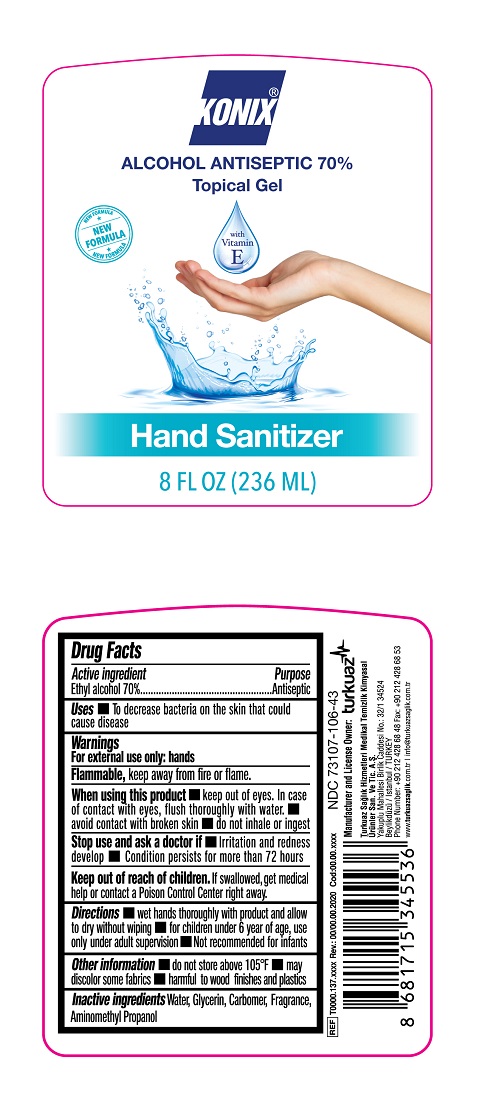 DRUG LABEL: Konix Hand Sanitizer Gel
NDC: 73107-106 | Form: GEL
Manufacturer: Turkuaz Saglik Hizmetleri Medikal Temizlik Kimyasal Urunler Sanayi ve Tic. AS
Category: otc | Type: HUMAN OTC DRUG LABEL
Date: 20220616

ACTIVE INGREDIENTS: ALCOHOL 70 mL/100 mL
INACTIVE INGREDIENTS: WATER; GLYCERIN; CARBOMER 940; AMINOMETHYLPROPANOL

KONIX Hand Sanitizer Gel

Active Ingredient

Ethyl alcohol 70%

Purpose

Antiseptic, Hand Sanitizer Gel

Use

To decrease bacteria on the skin that could cause disease

Warnings

For external use only: hands.

Flammable, keep away from fire or flame.

When using this product keep out of eyes. In case of contact with eyes, flush thoroughly with water. avoid contact with broken skin do not inhale or ingest

Stop use and ask a doctor if Irritation and redness develop Condition persists for more than 72 hours.

Keep out of reach of children.

If swallowed, get medical help or contact a Poison Control Center right away.

Directions

wet hands thoroughly with product and allow to dry without wiping

for children under 6 year of age, use only under adult supervision

Not recommended for infants

Other information

do not store above 105°F
may discolor some fabrics
harmful to wood finishes and plastics

Inactive Ingredients

Water, Glycerin, Carbomer, Fragrance, Aminomethyl Propanol